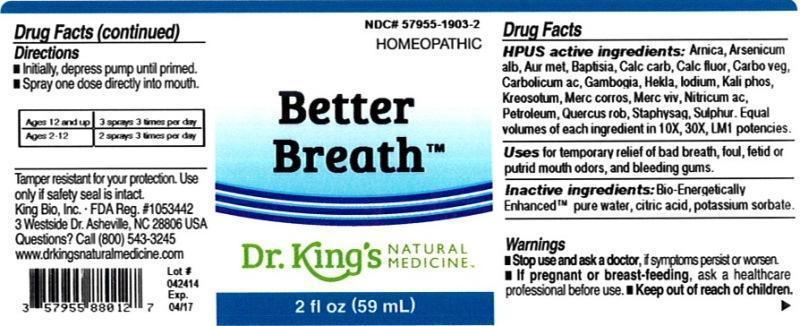 DRUG LABEL: Better Breath
NDC: 57955-1903 | Form: LIQUID
Manufacturer: King Bio Inc.
Category: homeopathic | Type: HUMAN OTC DRUG LABEL
Date: 20140505

ACTIVE INGREDIENTS: ARNICA MONTANA 10 [hp_X]/59 mL; ARSENIC TRIOXIDE 10 [hp_X]/59 mL; GOLD 10 [hp_X]/59 mL; BAPTISIA TINCTORIA ROOT 10 [hp_X]/59 mL; OYSTER SHELL CALCIUM CARBONATE, CRUDE 10 [hp_X]/59 mL; CALCIUM FLUORIDE 10 [hp_X]/59 mL; ACTIVATED CHARCOAL 10 [hp_X]/59 mL; PHENOL 10 [hp_X]/59 mL; GAMBOGE 10 [hp_X]/59 mL; HEKLA LAVA 10 [hp_X]/59 mL; IODINE 10 [hp_X]/59 mL; POTASSIUM PHOSPHATE, DIBASIC 10 [hp_X]/59 mL; WOOD CREOSOTE 10 [hp_X]/59 mL; MERCURIC CHLORIDE 10 [hp_X]/59 mL; MERCURY 10 [hp_X]/59 mL; NITRIC ACID 10 [hp_X]/59 mL; KEROSENE 10 [hp_X]/59 mL; QUERCUS ROBUR TWIG BARK 10 [hp_X]/59 mL; DELPHINIUM STAPHISAGRIA SEED 10 [hp_X]/59 mL; SULFUR 10 [hp_X]/59 mL
INACTIVE INGREDIENTS: WATER; CITRIC ACID MONOHYDRATE; POTASSIUM SORBATE

Better Breath™

ACTIVE INGREDIENT

Drug Facts__________________________________________________________________________________________________________

HPUS active ingredients: Arnica montana, Arsenicum album, Aurum metallicum, Baptisia tinctoria, Calcarea carbonica, Calcarea fluorica, Carbo vegetabilis, Carbolicum acidum, Gambogia, Hekla lava, Iodium, Kali phosphoricum, Kreosotum, Mercurius corrosivus, Mercurius vivus, Nitricum acidum, Petroleum, Quercus robur, Staphysagria, Sulphur. Equal volumes of each ingredient in 10X, 30X, LM1 potencies.

INDICATIONS AND USAGE

Uses for temporary relief of bad breath, foul, fetid or putrid mouth odors, and bleeding gums.

Inactive Ingredients:

Bio-Energetically Enhanced™ pure water, citric acid and potassium sorbate.

Warnings

- Stop use and ask your doctor if symptoms persist or worsen.
- If pregnant or breast-feeding, ask a healthcare professional before use.

- Keep out of reach of children.

Directions

- Initially, depress pump until primed.
- Spray one dose directly into mouth.
- Ages 12 and up: 3 sprays 3 times per day.
- Ages 2-12: 2 sprays 3 times per day

OTHER SAFETY INFORMATION

Tamper resistant for your protection. Use only if safety seal is intact.

PURPOSE

Uses for temporary relief of:

- bad breath
- foul
- fetid or putrid mouth odors
- bleeding gums